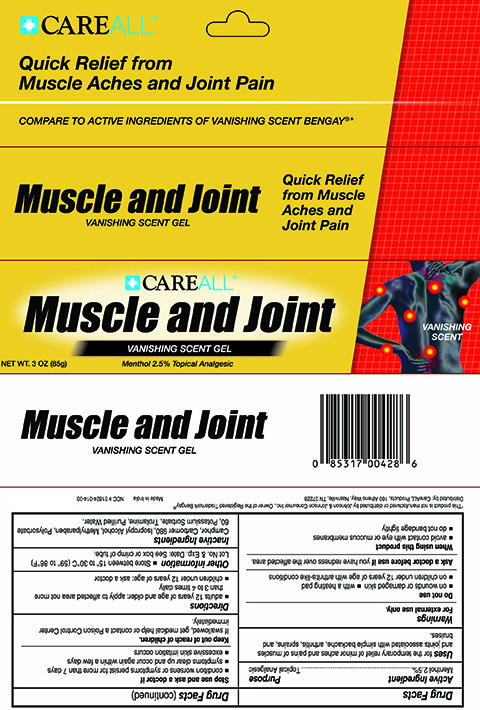 DRUG LABEL: CAREALL Musle and Joint
NDC: 51824-014 | Form: GEL
Manufacturer: New World Imports, Inc
Category: otc | Type: HUMAN OTC DRUG LABEL
Date: 20251201

ACTIVE INGREDIENTS: MENTHOL 25 mg/1 g
INACTIVE INGREDIENTS: CAMPHOR (SYNTHETIC); CARBOMER HOMOPOLYMER TYPE C; ISOPROPYL ALCOHOL; METHYLPARABEN; POLYSORBATE 60; POTASSIUM SORBATE; TROLAMINE; WATER

Drug Facts

ACTIVE INGREDIENT

Menthol 2.5%

PURPOSE

Topical Analegesic

Keep out of Reach of Children. If swallowed, get medical help of contact a Poison Control Center immediately.

INDICATIONS AND USAGE

For the temporary relief of minor aches and pains of muscles and joints associated with simple backache, arthritis, sprains, and bruises

WARNINGS

For External Use Only.

Do not use:

On wounds or damaged skin

With a heating pad

On children under 12 years of age with arthritis-like conditions

Ask a doctor before use if:

You have redness over the affected area

When using this product:

Avoid contact eith eyes or mucous membranes

Do not bandage tightly

Stop use and ask a Doctor if:

Condition worsens or symptoms persist for more than 7 days

Symptoms clear up and occur again within a few days

Excessive skin irritation occurs

DOSAGE AND ADMINISTRATION

Adults 12 years of age and older: apply to affected area not more than 3 to 4 times daily.

Children under 12 years of age: ask a doctor

INACTIVE INGREDIENT

Camphor, Carbomer 980, Isopropyl alcohol, Methylparaben, Polysorbate 60, Potassium Sorbate, Trolamine, Purified water